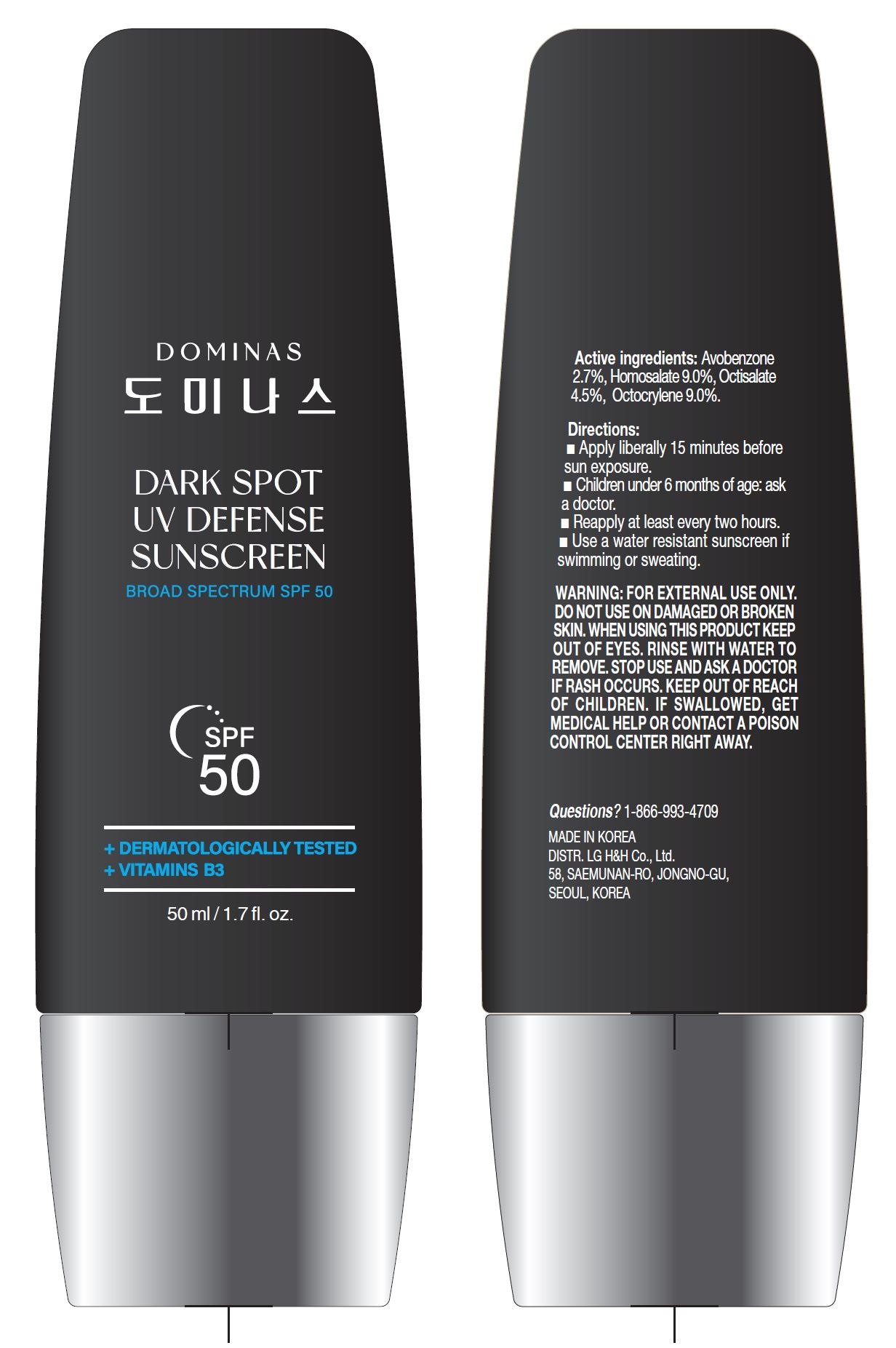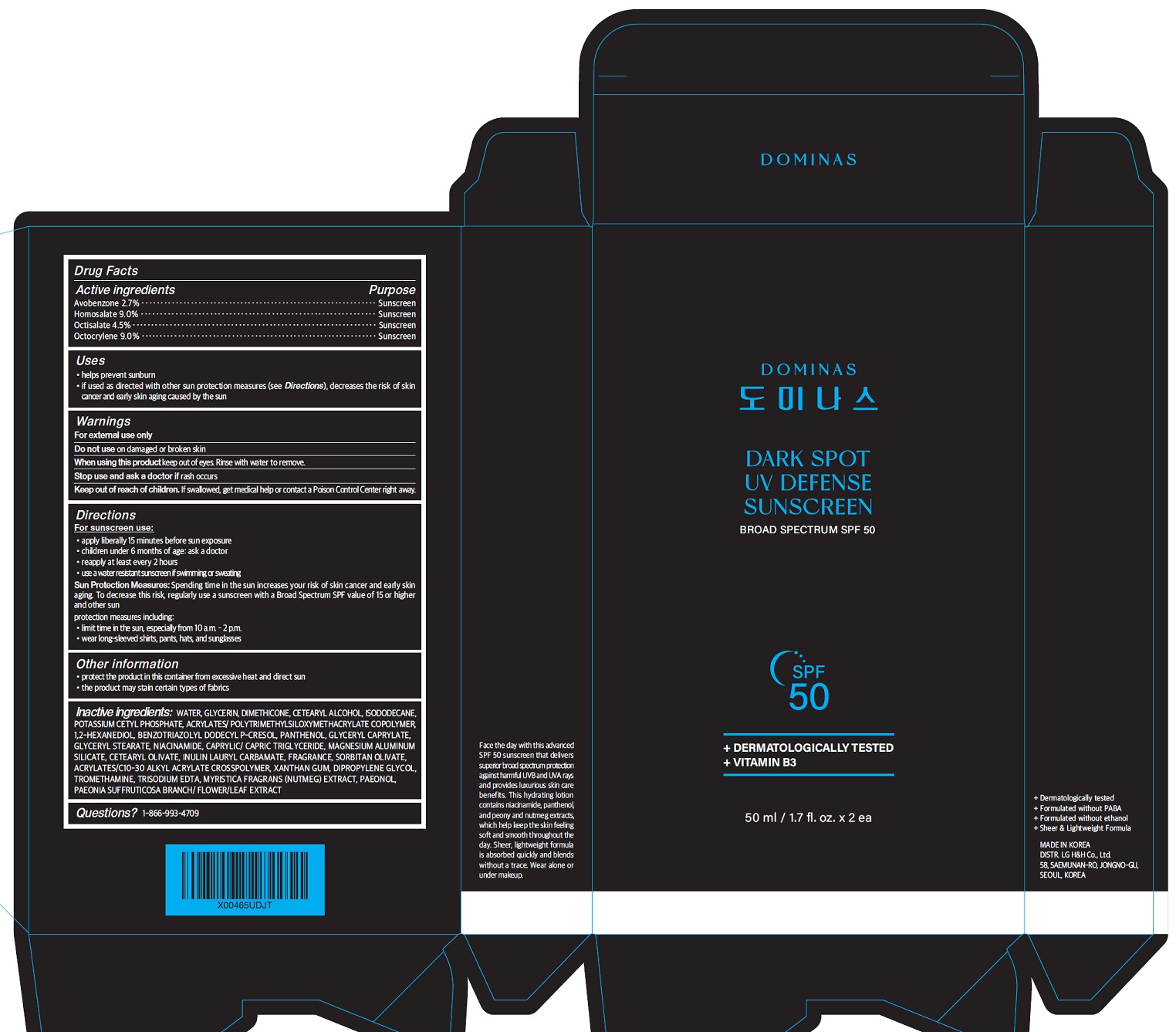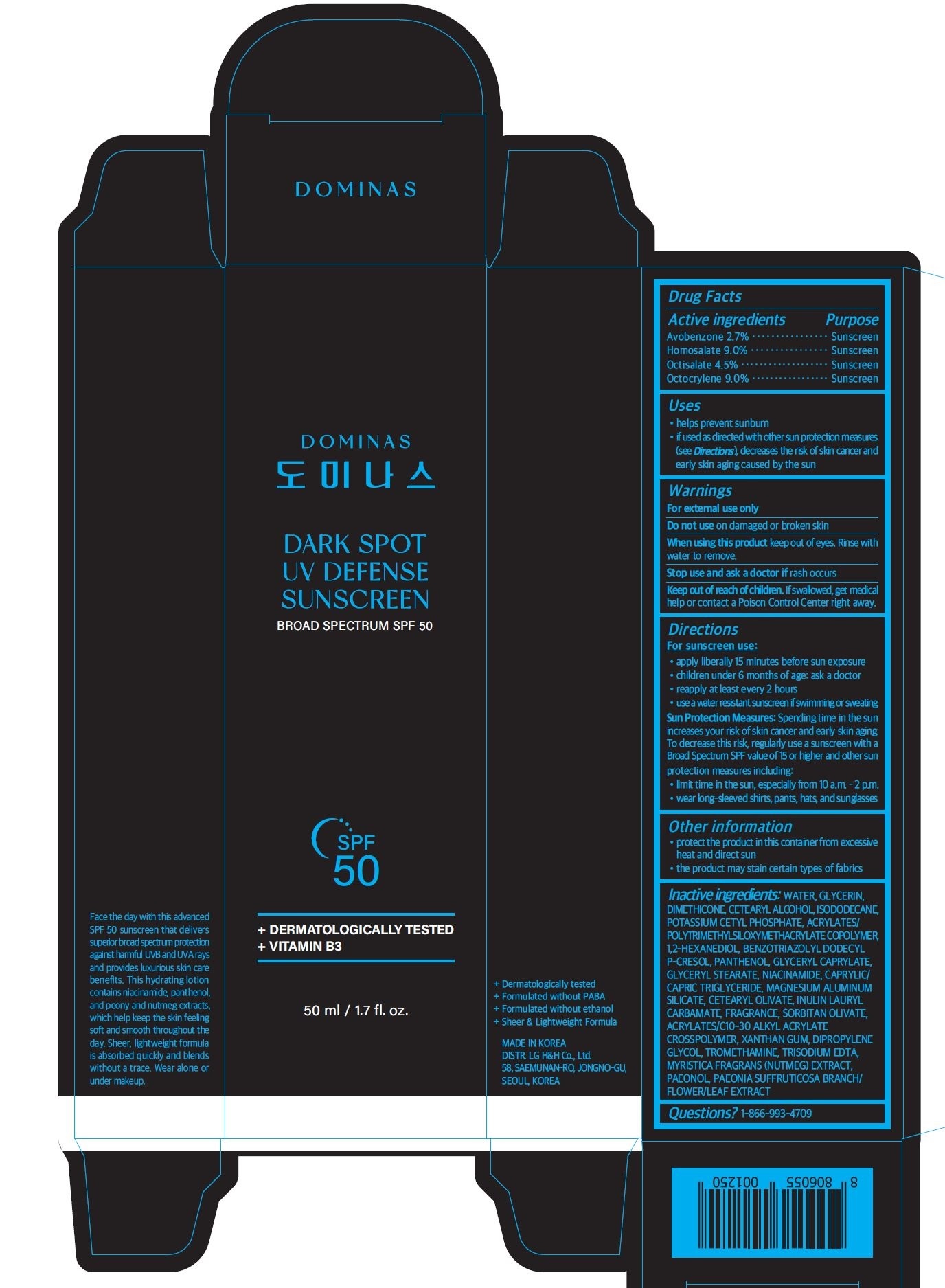 DRUG LABEL: Dominas Dark Spot UV Defense Sunscreen Broad Spectrum SPF 50
NDC: 53208-301 | Form: CREAM
Manufacturer: LG H&H Co.,Ltd.
Category: otc | Type: HUMAN OTC DRUG LABEL
Date: 20260105

ACTIVE INGREDIENTS: OCTISALATE 4.5 g/50 mL; HOMOSALATE 9 g/50 mL; AVOBENZONE 2.7 g/50 mL; OCTOCRYLENE 9 g/50 mL
INACTIVE INGREDIENTS: WATER

Dominas Dark Spot UV Defense Sunscreen Broad Spectrum SPF 50 (50mL)

ACTIVE INGREDIENTS

Avobenzone 2.7%
Homosalate 9.0%
Octisalate 4.5%
Octocrylene 9.0%

PURPOSE

Sunscreen

USES

- helps prevent sunburn
- if used as directed with other sun protection measures (see Directions), decreases the risk of skin cancer and early skin aging caused by the sun

WARNINGS

For external use only

Do not useon damaged or broken skin

WHEN USING

When using this productkeep out of eyes. Rinse with water to remove.

Stop use and ask doctorif rash occurs

Keep out of reach of children.If swallowed, get medical help or contact a Poison Control Center right away.

DIRECTIONS

- apply liberally 15 minutes before sun exposure
- children under 6 months: Ask a doctor
- reapply at least every 2 hours
- use a water resistant sunscreen if swimming or sweating
- Sun Protection Measures:Spending time in the sun increases your risk of skin cancer and early skin aging. To decrease this risk, regularly use a sunscreen with a Broad Spectrum SPF value of 15 or higher and other sun protection measures including:

- limit time in the sun, especially from 10 a.m. - 2 p.m.

- wear long-sleeved shirts, pants, hats, and sunglasses

INACTIVE INGREDIENTS

WATER, GLYCERIN, DIMETHICONE, CETEARYL ALCOHOL, ISODODECANE, POTASSIUM CETYL PHOSPHATE, ACRYLATES/POLYTRIMETHYLSILOXYMETHACRYLATE COPOLYMER, 1,2-HEXANEDIOL, BENZOTRIAZOLYL DODECYL P-CRESOL, PANTHENOL, GLYCERYL CAPRYLATE, GLYCERYL STEARATE, NIACINAMIDE, CAPRYLIC/CAPRIC TRIGLYCERIDE, MAGNESIUM ALUMINUM SILICATE, CETEARYL OLIVATE, INULIN LAURYL CARBAMATE, FRAGRANCE, SORBITAN OLIVATE, ACRYLATES/C10-30 ALKYL ACRYLATE CROSSPOLYMER, XANTHAN GUM, DIPROPYLENE GLYCOL, TROMETHAMINE,
TRISODIUM EDTA, MYRISTICA FRAGRANS (NUTMEG) EXTRACT, PAEONOL, PAEONIA SUFFRUTICOSA BRANCH/FLOWER/LEAF EXTRAC

OTHER INFORMATION

- protect the product in this container from excessive heat and direct sun
- the product may stain certain types of fabrics

QUESTIONS?

1-866-993-4709

PRINCIPAL DISPLAY PANEL 50ml / 1.7 fl. oz Tube Carton

DOMINAS

DARK SPOT
UV DEFENSE
SUNSCREEN

BROAD SPECTRUM SPF 50

+ DERMATOLOGICALLY TESTED
+ VITAMIN B3
50 ml / 1.7 fl. oz
+ Dermatologically tested
+ Formulated without PABA
+ Fomulated without ethanol
+ Sheer & Lightweight Formula
MADE IN KOREA
DISTR. LG H&H Co., Ltd.
58, SAEMUNAN-RO, JONGNO-GU,
SEOUL, KOREA

PRINCIPAL DISPLAY PANEL 50ml / 1.7 fl. oz x 2 ea

DOMINAS

DARK SPOT
UV DEFENSE
SUNSCREEN

BROAD SPECTRUM SPF 50

+ DERMATOLOGICALLY TESTED
+ VITAMIN B3

50 ml / 1.7 fl. oz x 2 ea

+ Dermatologically tested
+ Formulated without PABA
+ Fomulated without ethanol
+ Sheer & Lightweight Formula

MADE IN KOREA
DISTR. LG H&H Co., Ltd.
58, SAEMUNAN-RO, JONGNO-GU,
SEOUL, KOREA